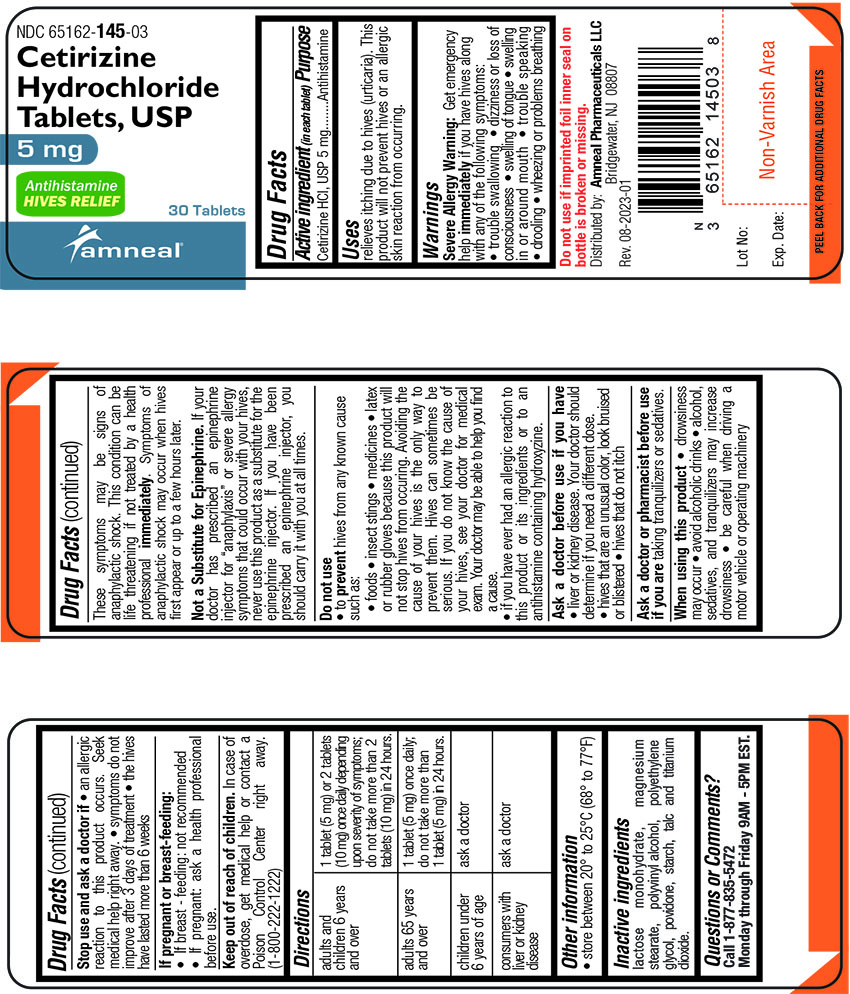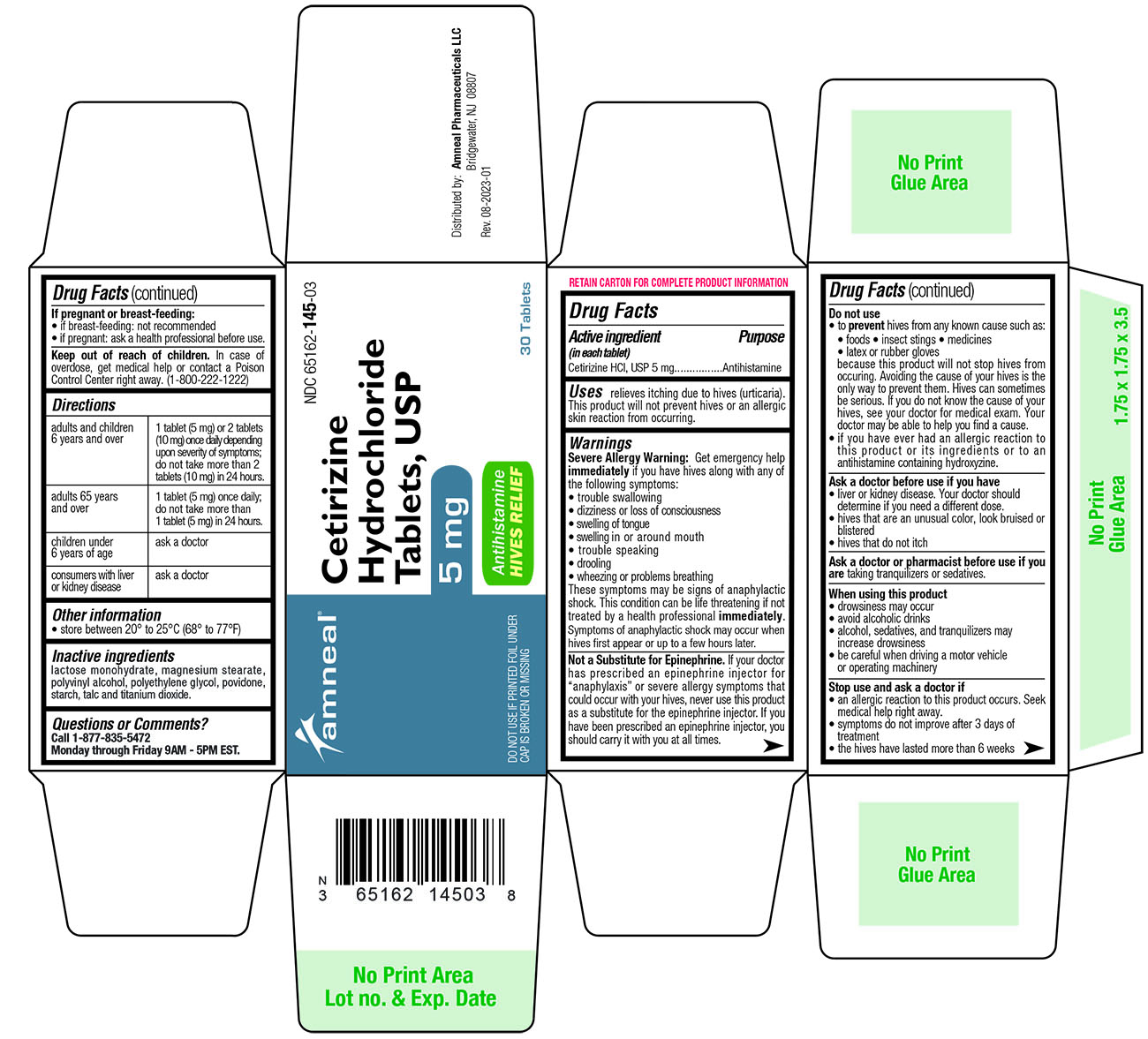 DRUG LABEL: Cetirizine Hydrochloride
NDC: 65162-145 | Form: TABLET
Manufacturer: Amneal Pharmaceuticals LLC
Category: otc | Type: HUMAN OTC DRUG LABEL
Date: 20241023

ACTIVE INGREDIENTS: CETIRIZINE HYDROCHLORIDE 5 mg/1 1
INACTIVE INGREDIENTS: LACTOSE MONOHYDRATE; MAGNESIUM STEARATE; POLYVINYL ALCOHOL, UNSPECIFIED; POLYETHYLENE GLYCOL, UNSPECIFIED; POVIDONE; STARCH, CORN; TALC; TITANIUM DIOXIDE

CETIRIZINE HYDROCHLORIDE TABLETS

Drug Facts

ACTIVE INGREDIENT

(in each tablet)

Cetirizine HCl, USP 5 mg

PURPOSE

Antihistamine

INDICATIONS AND USAGE

Relieves itching due to hives (urticaria). This product will not prevent hives or an allergic skin reaction from occurring.

WARNINGS

Severe Allergy Warning: Get emergency help immediately if you have hives along

with any of the following symptoms:

• trouble swallowing

• dizziness or loss of consciousness

• swelling of tongue

• swelling in or around mouth

• trouble speaking

• drooling

• wheezing or problems breathing

These symptoms may be signs of anaphylactic shock. This condition can be life threatening if not treated by a health professional immediately. Symptoms of anaphylactic shock may occur when hives first appear or up to a few hours later.

Not a Substitute for Epinephrine . If your doctor has prescribed an epinephrine injector for “anaphylaxis” or severe allergy symptoms that could occur with your hives, never use this product as a substitute for the epinephrine injector. If you have been prescribed an epinephrine injector, you should carry it with you at all times.

DO NOT USE

• to prevent hives from any known cause such as:

• foods • insect stings • medicines • latex or rubber gloves

because this product will not stop hives from occurring. Avoiding the cause of your hives is the only way to prevent them. Hives can sometimes be serious. If you do not know the cause of your hives, see your doctor for medical exam. Your doctor may be able to help you find a cause.

• if you have ever had an allergic reaction to this product or its ingredients or to an antihistamine containing hydroxyzine.

ASK DOCTOR

Ask a doctor before use if you have

• liver or kidney disease. Your doctor should determine if you need a different dose.

• hives that are an unusual color, look bruised or blistered

• hives that do not itch

ASK DOCTOR/PHARMACIST

Ask a doctor of pharmacist before use if you are taking tranquilizers or sedatives.

WHEN USING

When using this product

• drowsiness may occur

• avoid alcoholic drinks

• alcohol, sedatives, and tranquilizers may increase drowsiness

• be careful when driving a motor vehicle or operating machinery

STOP USE

Stop use and ask a doctor if

• an allergic reaction to this product occurs. Seek medical help right away.

• symptoms do not improve after 3 days of treatment

• the hives have lasted more than 6 weeks

PREGNANCY OR BREAST FEEDING

If pregnant or breast-feeding:

• if breast-feeding: not recommended

• if pregnant: ask a health professional before use.

Keep out of reach of children. In case of overdose, get medical help or contact a Poison Control Center right away. (1-800-222-1222)

DIRECTIONS

Adults and children 6years and over | 1 tablet (5 mg) or 2 tablets (10 mg) once daily depending upon severity of symptoms; do not take more than 2 tablets (10 mg) in 24 hours.
Adults 65years and over | 1 tablet (5 mg) once daily; do not take more than 1 tablet (5 mg) in 24 hours.
Children under 6 years of age | ask a doctor
Consumers with liver or kidney disease | ask a doctor

OTHER INFORMATION

• store between 20° to 25°C (68° to 77°F)

INACTIVE INGREDIENTS

lactose monohydrate, magnesium stearate, polyvinyl alcohol, polyethylene glycol, povidone, starch, talc and titanium dioxide.

OTC - QUESTIONS

Questions or Comments?

Call 1-877-835-5472

Monday through Friday 9AM - 5PM EST.

Distributed by:
Amneal Pharmaceuticals LLC
Bridgewater, NJ 08807

Rev. 08-2023-01